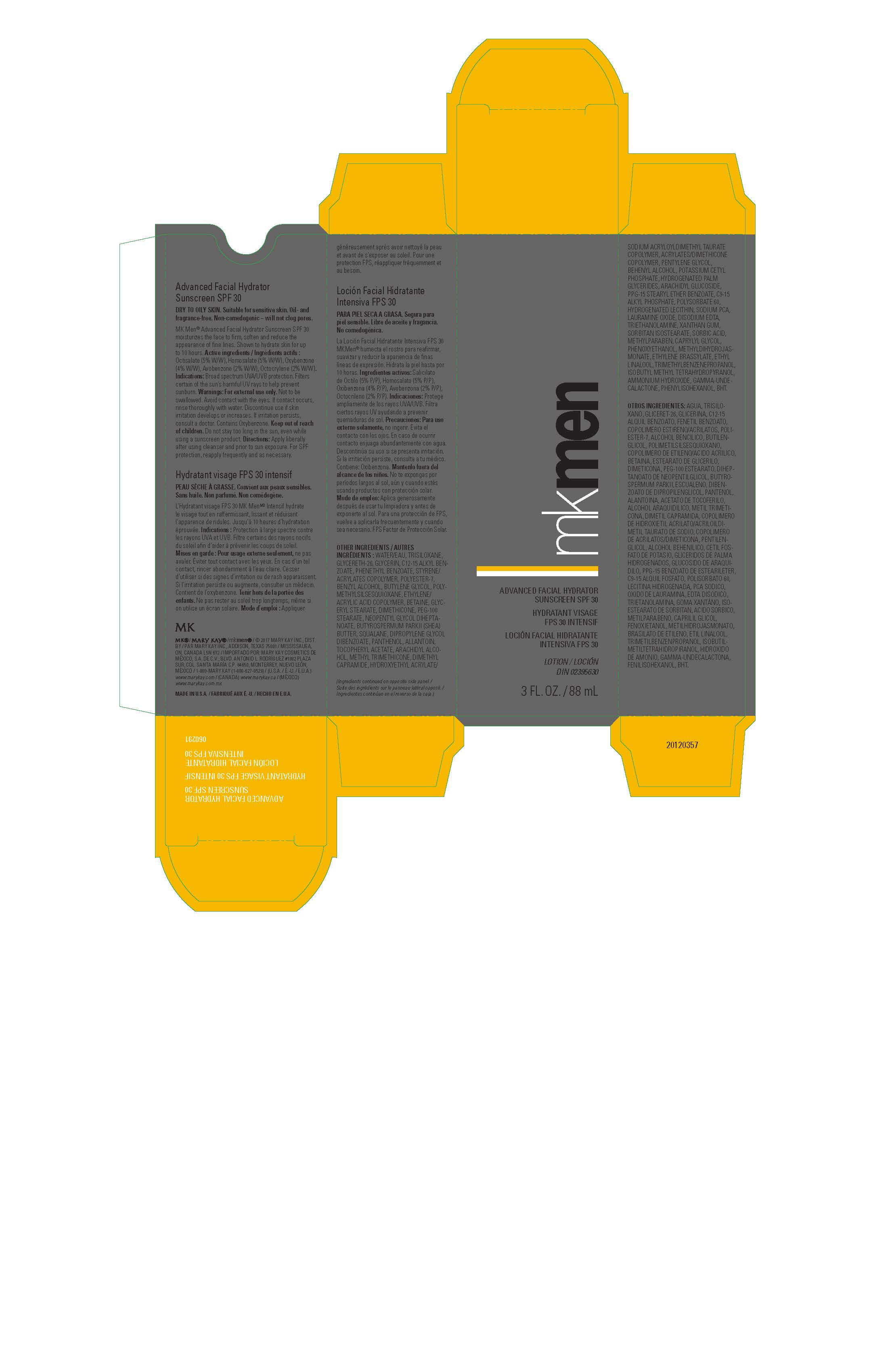 DRUG LABEL: MK Men Advanced Facial Hydrator Sunscreen SPF 30
NDC: 51531-0291 | Form: LOTION
Manufacturer: Mary Kay Inc.
Category: otc | Type: HUMAN OTC DRUG LABEL
Date: 20200824

ACTIVE INGREDIENTS: AVOBENZONE 2 g/100 mL; HOMOSALATE 5 g/100 mL; OCTOCRYLENE 2 g/100 mL; OCTISALATE 5 g/100 mL; OXYBENZONE 4 g/100 mL
INACTIVE INGREDIENTS: WATER; GLYCERETH-26; DIMETHICONE; GLYCERIN; ALKYL (C12-15) BENZOATE; PHENETHYL BENZOATE; TRISILOXANE; POLYESTER-7; BENZYL ALCOHOL; BETAINE; BUTYLENE GLYCOL; ACRYLIC ACID/ETHYLENE COPOLYMER (600 MPA.S); POLYMETHYLSILSESQUIOXANE (4.5 MICRONS); GLYCERYL MONOSTEARATE; NEOPENTYL GLYCOL DIHEPTANOATE; PHENOXYETHANOL; DIPROPYLENE GLYCOL DIBENZOATE; HYDROXYETHYL ACRYLATE/SODIUM ACRYLOYLDIMETHYL TAURATE COPOLYMER (45000 MPA.S AT 1%); PEG-100 STEARATE; CAPRYLYL GLYCOL; ARACHIDYL ALCOHOL; METHYL TRIMETHICONE; DIMETHYL CAPRAMIDE; SQUALANE; SHEA BUTTER; PENTYLENE GLYCOL; DOCOSANOL; POTASSIUM CETYL PHOSPHATE; XANTHAN GUM; LAURAMINE OXIDE; EDETATE DISODIUM; HYDROGENATED PALM GLYCERIDES; METHYLPARABEN; ARACHIDYL GLUCOSIDE; PPG-15 STEARYL ETHER BENZOATE; POLYSORBATE 60; HYDROGENATED SOYBEAN LECITHIN; PANTHENOL; .ALPHA.-TOCOPHEROL ACETATE; SORBIC ACID; ALLANTOIN; METHYL DIHYDROJASMONATE (SYNTHETIC); BUTYLATED HYDROXYTOLUENE; SODIUM PYRROLIDONE CARBOXYLATE; TROLAMINE; SORBITAN ISOSTEARATE; ETHYLENE BRASSYLATE; ETHYL LINALOOL; TRIMETHYLBENZENEPROPANOL; 2-ISOBUTYL-4-METHYLTETRAHYDROPYRAN-4-OL; AMMONIA; .GAMMA.-UNDECALACTONE; PHENYLISOHEXANOL

MK Men SPF 30 Sunscreen CA/LATAM Export Only

ACTIVE INGREDIENTS:

AVOBENZONE (2% W/W)

HOMOSALATE (5% W/W)

OCTISALATE (5% W/W)

OCTOCRYLENE (2% W/W)

OXYBENZONE (4% W/W)

Indications:

Broad spectrum UVA/UVB protection.

Filters certain of the sun's harmful UV rays to help prevent sunburn.

Warnings:

For external use only, not to be swallowed.

Avoid contact with the eyes.

If contact occurs, rinse thoroughly with water.

Discontinue use if skin irritation develops or increases.

If irritation persists, consult a doctor.

Contains Oxybenzone.

Keep out of the reach of children.

Do not stay too long in the sun, even while using a sunscreen product.

Directions:

Apply liberally after using cleanser and prior to sun exposure.

For SPF protection, reapply frequently and as necessary.

Principal Display Panel - 88 mL carton

MK Men

ADVANCED FACIAL HYDRATOR
SUNSCREEN SPF 30
HYDRATANT VISAGE
FPS 30 INTENSIF
LOCIÓN FACIAL HIDRATANTE
INTENSIVA FPS 30
LOTION / LOCIÓN
DIN 02395630

3 FL. OZ. / 88 mL